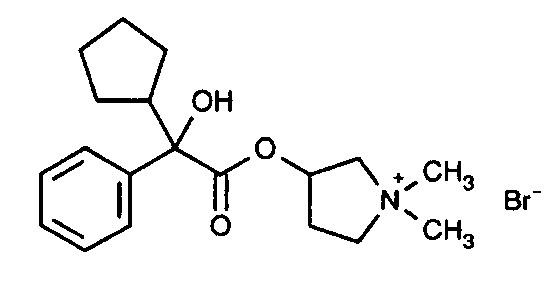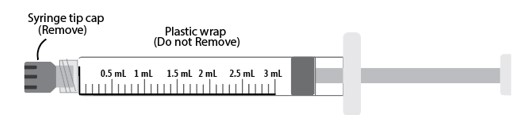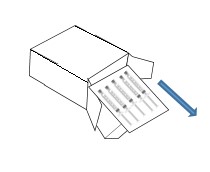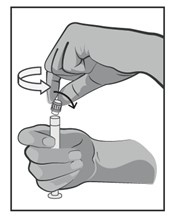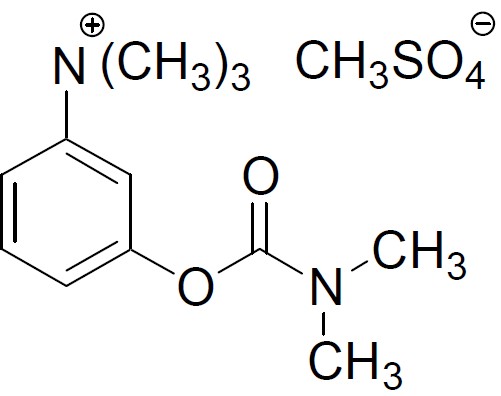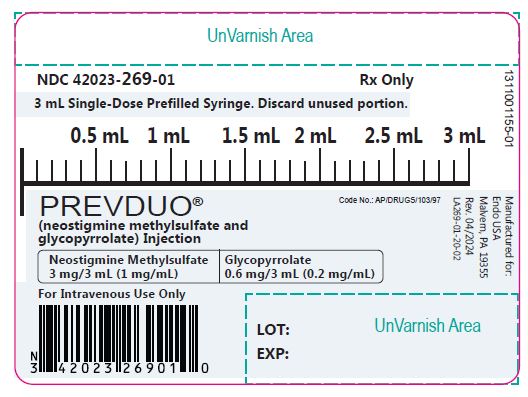 DRUG LABEL: PREVDUO
NDC: 42023-269 | Form: INJECTION
Manufacturer: Endo USA
Category: prescription | Type: Human Prescription Drug Label
Date: 20240410

ACTIVE INGREDIENTS: NEOSTIGMINE METHYLSULFATE 1 mg/1 mL; GLYCOPYRROLATE 0.2 mg/1 mL
INACTIVE INGREDIENTS: EDETATE DISODIUM; SODIUM CHLORIDE; HYDROCHLORIC ACID; SODIUM HYDROXIDE; WATER; NITROGEN

HIGHLIGHTS OF PRESCRIBING INFORMATION

These highlights do not include all the information needed to use PREVDUO® safely and effectively. See full prescribing information for PREVDUO®.
PREVDUO® (neostigmine methylsulfate and glycopyrrolate) injection, for intravenous use
Initial U.S. Approval: 2023

1 INDICATIONS AND USAGE

PREVDUO®, a fixed dose combination of a cholinesterase inhibitor and antimuscarinic agent, is indicated in patients age two years and above for the reversal of the effects of non-depolarizing neuromuscular blocking agents (NMBAs) after surgery, while decreasing the peripheral muscarinic effects (e.g., bradycardia and excessive secretions) associated with cholinesterase inhibition following NMBA reversal administration (1).

2 DOSAGE AND ADMINISTRATION

• Should be administered by trained healthcare providers (2.1)
• Peripheral nerve stimulator and monitoring for twitch responses should be used to determine when PREVDUO® should be initiated and if additional doses are needed (2.2)
• For reversal of NMBAs with shorter half-lives in patients age 2 years and up, when first twitch response is substantially greater than 10% of baseline, or when a second twitch is present: 0.03 mg/kg of neostigmine methylsulfate (0.006 mg/kg of glycopyrrolate) by intravenous route (2.2)
• For reversal of NMBAs with longer half-lives or when first twitch response is close to 10% of baseline in patients age 2 years and up: 0.07 mg/kg of neostigmine methylsulfate (0.014 mg/kg of glycopyrrolate) by intravenous route (2.2)
• Maximum total dosage is 0.07 mg/kg of neostigmine methylsulfate or up to a total of 5 mg neostigmine methylsulfate (whichever is less) (2.2)

3 DOSAGE FORMS AND STRENGTHS

Injection: Clear, colorless solution available as 3 mg/3 mL of neostigmine methylsulfate and 0.6 mg/3 mL of glycopyrrolate (1 mg/mL of neostigmine methylsulfate and 0.2 mg/mL of glycopyrrolate) in a single-dose 3 mL Prefilled Syringe. (3)

4 CONTRAINDICATIONS

• Hypersensitivity to neostigmine, glycopyrrolate, or nonactive ingredients (4)
• Peritonitis or mechanical obstruction of the intestinal or urinary tract (4)
• Patients with glaucoma; obstructive uropathy; obstructive disease of the gastrointestinal tract; paralytic ileus, intestinal atony of the elderly or debilitated patient; unstable cardiovascular status in acute hemorrhage; severe ulcerative colitis; toxic megacolon complicating ulcerative colitis; myasthenia gravis (4).

5 WARNINGS AND PRECAUTIONS

• Bradycardia: consideration should be given to administration of glycopyrrolate prior to neostigmine (i.e., as separate products) in patients with bradycardia or in patients in whom bradycardia, a known risk of neostigmine methysulfate, may cause hemodynamic instability. (5.1)
• Serious Reactions with Coexisting Conditions: Use with caution in patients with, coronary artery disease, cardiac arrhythmias, recent acute coronary syndrome, hyperthyroidism or myasthenia gravis. (5.2)
• Hypersensitivity: Because of the possibility of hypersensitivity, medications to treat anaphylaxis should be readily available. (5.3)
• Neuromuscular Dysfunction: Can occur if large doses of PREVDUO® are administered when neuromuscular blockade is minimal; reduce dose if recovery from neuromuscular blockade is nearly complete. (5.4)
• Cholinergic Crisis: It is important to differentiate between myasthenic crisis and cholinergic crisis caused by overdosage of neostigmine. (5.5)
• Precipitation of Acute Glaucoma: Glycopyrrolate may cause mydriasis and increase intraocular pressure in patients with glaucoma. Advise patients with glaucoma to promptly seek medical care if they experience symptoms of acute angle closure glaucoma. (5.6)
• Drowsiness and Blurred Vision: Warn patients about participating in activities requiring mental alertness. (5.7)
• Heat Prostration: Advise patients to avoid exertion and high environmental temperatures after receiving PREVDUO®. (5.8)
• Intestinal Obstruction: Diarrhea may be an early symptom of incomplete intestinal obstruction. Avoid use in patients with diarrhea and ileostomy or colostomy. (5.9)
• Tachycardia: Increase in heart rate may occur. Use with caution in patients with coronary artery disease, congestive heart failure, cardiac arrhythmias, hypertension, or hyperthyroidism. (5.10)

6 ADVERSE REACTIONS

• Most common adverse reactions to neostigmine during treatment: bradycardia, nausea, vomiting, blurred vision and photophobia. (6)
• Most common adverse reactions to glycopyrrolate are related to anticholinergic pharmacology and may include xerostomia (dry mouth); urinary hesitancy and retention; blurred vision and photophobia due to mydriasis (dilation of the pupil); cycloplegia; increased ocular tension; tachycardia; bradycardia; palpitation; and decreased sweating. (6)

To report SUSPECTED ADVERSE REACTIONS, contact Endo at 1-800-828-9393 or FDA at 1-800-FDA-1088 or www.fda.gov/medwatch.

7 DRUG INTERACTIONS

The concurrent use of glycopyrrolate with other anticholinergics or medications with anticholinergic activity may intensify the antimuscarinic effects and may result in an increase in anticholinergic side effects. (7)

FULL PRESCRIBING INFORMATION

1 INDICATIONS AND USAGE

PREVDUO®, a fixed dose combination of cholinesterase inhibitor and antimuscarinic agent, is indicated in patients age two years and above for the reversal of the effects of nondepolarizing neuromuscular blocking agents (NMBA) after surgery, while decreasing the peripheral muscarinic effects (e.g., bradycardia and excessive secretions) associated with cholinesterase inhibition following NMBA reversal administration.

2 DOSAGE AND ADMINISTRATION

2.1 Important Dosage and Administration Information

• PREVDUO® should be administered by trained healthcare providers familiar with the use, actions, characteristics, and complications of neuromuscular blocking agents (NMBA) and neuromuscular block reversal agents. Doses of PREVDUO® should be individualized, and a peripheral nerve stimulator should be used to determine the time of initiation of PREVDUO® and should be used to determine the need for additional doses.
• PREVDUO® is for intravenous use only and should be injected slowly over a period of at least 1 minute. The PREVDUO® dosage is weight-based [see Dosage and Administration (2.2)].
• Prior to PREVDUO® administration and until complete recovery of normal ventilation, the patient should be well ventilated and a patent airway maintained. Satisfactory recovery should be judged by adequacy of skeletal muscle tone and respiratory measurements in addition to the response to peripheral nerve stimulation.
• Peripheral nerve stimulation devices capable of delivering a train-of-four (TOF) stimulus are essential to effectively using PREVDUO®.
• There must be a twitch response to the first stimulus in the TOF of at least 10% of its baseline level, i.e., the response prior to NMBA administration, prior to the administration of PREVDUO®.
• Prior to administration, visually inspect PREVDUO® for particulate matter and discoloration.
• TOF monitoring should continue to be used to evaluate the extent of recovery of neuromuscular function and the possible need for an additional dose of PREVDUO®.
• TOF monitoring alone should not be relied upon to determine the adequacy of reversal of neuromuscular blockade as related to a patient’s ability to adequately ventilate and maintain a patent airway following tracheal extubation.
• Patients should continue to be monitored for adequacy of reversal from NMBAs for a period of time that would assure full recovery based on the patient’s medical condition and the pharmacokinetics of neostigmine and the NMBA used.

2.2 Dosage in Adults

A 0.03 mg/kg to 0.07 mg/kg dose of Neostigmine methylsulfate (0.006 mg/kg to 0.014 mg/kg dose of Glycopyrrolate) Injection will generally achieve a TOF twitch ratio of 90% (TOF0.9) within 10 to 20 minutes of administration, with minimization of neostigmine-induced bradycardia due to the included 0.2 mg of glycopyrrolate per 1 mg neostigmine. Dose selection should be based on the extent of spontaneous recovery that has occurred at the time of administration, the half-life of the NMBA being reversed, and whether there is a need to rapidly reverse the NMBA.

• The 0.03 mg/kg dose of neostigmine methylsulfate (0.006 mg/kg of glycopyrrolate) is recommended for:
• Reversal of NMBAs with shorter half-lives, e.g., rocuronium, or
• When the first twitch response to the TOF stimulus is substantially greater than 10% of baseline or when a second twitch is present.
• The 0.07 mg/kg dose of neostigmine methylsulfate (0.014 mg/kg of glycopyrrolate) dose is recommended for:
• Reversal of NMBAs with longer half-lives, e.g., vecuronium and pancuronium, or
• When the first twitch response is relatively weak, i.e., not substantially greater than 10% of baseline or
• There is need for more rapid recovery
The recommended maximum total dose is 0.07 mg/kg of neostigmine methylsulfate or up to a total of 5 mg of neostigmine methylsulfate, whichever is less.

2.3 Dosage in Pediatric Patients age 2 years and above

For pediatric population age >2 years, adult guidelines should be followed when PREVDUO® is administered. Pediatric patients require PREVDUO® doses similar to those for adult patients.
PREVDUO® is not recommended for use in pediatric patients less than 2 years of age, as the blood pressure in pediatric patients, particularly infants and neonates, is sensitive to changes in heart rate [see Use in Specific Populations (8.4)].

2.4 Instructions for Use (Administration Technique)

a) Inspect the outer carton for:
- absence of external particles
- drug product name
- dosage form
- drug strength
- fill volume
- route of administration
- expiration date
b) Take out the plastic tray from the outer carton and remove the prefilled syringe from tray.

c) Perform visual inspection of the prefilled syringe for:
- absence of physical damage to syringe
- absence of external particles
- absence of internal particles (particulate matter)
- discoloration
- drug product name
- drug strength
- fill volume
- expiration date
d) Remove tip cap by twisting off

e) Discard the tip cap.
f) Expel the air bubble by pushing the plunger rod. Adjust the dose (if applicable).
g) Connect the prefilled syringe to an appropriate intravenous connection. Ensure that the prefilled syringe is securely attached to the needle or needleless luer access device (NLAD).
h) Press the plunger rod slowly to deliver the medication through needle or needleless luer access device (NLAD) over a period of at least 1 minute. Ensure that appropriate pressure is maintained on the plunger rod during the entire administration.
i) Remove the prefilled syringe from needle or needleless luer access device (NLAD) and discard into appropriate receptacle.
When needle is connected to syringe, to prevent needle-stick injuries, needles should not be recapped.
NOTES:
- All steps given in the ‘instructions for use’ must be performed sequentially
- Do not re-sterilize the syringe
- Do not use this product on a sterile field
- Do not introduce any other fluid into the syringe at any time
- This product is for single use only

3 DOSAGE FORMS AND STRENGTHS

PREVDUO® is a clear, colorless solution available as:
• Injection: 3 mg/3 mL of neostigmine methylsulfate and 0.6 mg/3 mL of glycopyrrolate (1 mg/mL of neostigmine methylsulfate and 0.2 mg/mL of glycopyrrolate) in a single-dose 3 mL prefilled syringe.

4 CONTRAINDICATIONS

PREVDUO® is contraindicated in patients with:
• known hypersensitivity to neostigmine methylsulfate (known hypersensitivity reactions have included urticaria, angioedema, erythema multiforme, generalized rash, facial swelling, peripheral edema, pyrexia, flushing, hypotension, bronchospasm, bradycardia and anaphylaxis) and glycopyrrolate or any inactive ingredients [see Warnings and Precautions (5.3)].
• peritonitis or mechanical obstruction of the intestinal or urinary tract.
• Glaucoma; obstructive uropathy (for example, bladder neck obstruction due to prostatic hypertrophy); obstructive disease of the gastrointestinal tract (as in achalasia, pyloroduodenal stenosis, etc.); paralytic ileus, intestinal atony of the elderly or debilitated patient; unstable cardiovascular status in acute hemorrhage; severe ulcerative colitis; toxic megacolon complicating ulcerative colitis; myasthenia gravis.

5 WARNINGS AND PRECAUTIONS

5.1 Bradycardia

Neostigmine, a component of PREVDUO®, is associated with bradycardia. Consideration should be given to administration of glycopyrrolate prior to neostigmine (i.e., as separate products) in patients with bradycardia or in patients in whom bradycardia, a known risk of neostigmine methysulfate, may cause hemodynamic instability.

5.2 Serious Adverse Reactions in Patients with Certain Coexisting Conditions

PREVDUO® should be used with caution in patients with coronary artery disease, congestive heart failure, cardiac arrhythmias, recent acute coronary syndrome, hypertension, myasthenia gravis and hyperthyroidism. Because of the known pharmacology of neostigmine methylsulfate as an acetylcholinesterase inhibitor, cardiovascular effects such as bradycardia, hypotension or dysrhythmia would be anticipated. In patients with acute cardiovascular conditions such as coronary artery disease, cardiac arrhythmias or recent acute coronary syndrome, the risk of blood pressure and heart rate complications may be increased. Risk of these complications may also be increased in patients with myasthenia gravis.

5.3 Hypersensitivity

Because of the possibility of hypersensitivity, medications to treat anaphylaxis should be readily available.

5.4 Neuromuscular Dysfunction

Large doses of PREVDUO® administered when neuromuscular blockade is minimal can produce neuromuscular dysfunction. The dose of PREVDUO® should be reduced if recovery from neuromuscular blockade is nearly complete.

5.5 Cholinergic Crisis

It is important to differentiate between myasthenic crisis and cholinergic crisis caused by overdosage of neostigmine. Both conditions result in extreme muscle weakness but require radically different treatment. [see Overdosage (10)].

5.6 Precipitation of Acute Glaucoma

Glycopyrrolate, a component of PREVDUO®, is contraindicated in patients with glaucoma because it may cause mydriasis and increase intraocular pressure. Advise patients with glaucoma to promptly seek medical care in the event that they experience symptoms of acute angle closure glaucoma (pain and reddening of the eyes, accompanied by dilated pupils).

5.7 Drowsiness and Blurred Vision

Glycopyrrolate, a component of PREVDUO®, may cause drowsiness or blurred vision. Warn patients not to participate in activities requiring mental alertness, such as operate a motor vehicle or other machinery or perform hazardous work until these issues resolve.

5.8 Heat Prostration

Glycopyrrolate, a component of PREVDUO®, may cause heat prostration (due to decreased sweating) in presence of fever, high environmental temperature, and/or during physical exercise, particularly in children and the elderly. Advise patients to avoid exertion and high environmental temperature after receiving PREVDUO®.

5.9 Intestinal Obstruction

Diarrhea may be an early symptom of incomplete intestinal obstruction, especially in patients with ileostomy or colostomy. In this instance treatment with Glycopyrrolate, a component of PREVDUO® is inappropriate and possibly harmful. Avoid use in patients with these conditions.

5.10 Tachycardia

Investigate any tachycardia before giving Glycopyrrolate, a component of PREVDUO® because an increase in the heart rate may occur. Use with caution in patients with coronary artery disease, congestive heart failure, cardiac arrhythmias, hypertension, or hyperthyroidism.

6 ADVERSE REACTIONS

6.1 Clinical Trials Experience

Neostigmine Methylsulfate
Because clinical trials are conducted under widely varying conditions, adverse reaction rates observed in the clinical trials of a drug cannot be directly compared to rates in the clinical trials of another drug and may not reflect the rates observed in practice.
Adverse reactions to neostigmine methylsulfate are most often attributable to exaggerated pharmacological effects, in particular, at muscarinic receptor sites. The addition of glycopyrrolate to the neostigmine-glycopyrrolate prefilled syringe may prevent or mitigate these reactions.
Quantitative adverse event data are available from trials of neostigmine methylsulfate in which 200 adult patients were exposed to the product. The following table lists the adverse reactions that occurred with an overall frequency of 1% or greater.

System Organ Class | Adverse Reaction
Cardiovascular Disorders | bradycardia, hypotension, tachycardia/heart rate increase
Gastrointestinal Disorders | dry mouth, nausea, post-procedural nausea, vomiting
General Disorders and Administration Site Conditions | incision site complication, pharyngolaryngeal pain, procedural complication, procedural pain
Nervous System Disorders | dizziness, headache, postoperative shivering, prolonged neuromuscular blockade
Psychiatric Disorders | Insomnia
Respiratory, Thoracic and Mediastinal Disorders | dyspnea, oxygen desaturation < 90%
Skin and Subcutaneous Tissue Disorders | Pruritus

Glycopyrrolate

Because clinical trials are conducted under widely varying conditions, adverse reaction rates observed in the clinical trials of a drug cannot be directly compared to rates in the clinical trials of another drug and may not reflect the rates observed in practice.
Anticholinergics, including glycopyrrolate, can produce certain effects, most of which are extensions of their pharmacologic actions. Adverse reactions may include xerostomia (dry mouth); urinary hesitancy and retention; blurred vision and photophobia due to mydriasis (dilation of the pupil); cycloplegia; increased ocular tension; tachycardia; palpitation; decreased sweating; loss of taste; headache; nervousness; drowsiness; weakness; dizziness; insomnia; nausea; vomiting; impotence; suppression of lactation; constipation; bloated feeling; severe allergic reactions including anaphylactic/anaphylactoid reactions; hypersensitivity; urticaria, pruritus, dry skin, and other dermal manifestations; some degree of mental confusion and/or excitement, especially in elderly persons.

6.2 Post Marketing Experience

Neostigmine Methylsulfate
The following adverse reactions have been identified during post-approval parenteral use of neostigmine methylsulfate. Because these reactions are reported voluntarily from a population of uncertain size, it is not always possible to reliably estimate their frequency or establish a causal relationship to drug exposure.

System Organ Class | Adverse Reaction
Allergic Disorders | allergic reactions, anaphylaxis
Nervous System Disorders | convulsions, drowsiness, dysarthria, fasciculation, loss of consciousness, miosis, visual changes
Cardiovascular Disorders | cardiac arrest, cardiac arrhythmias (A-V block, nodal rhythm), hypotension, nonspecific EKG changes, syncope
Respiratory, Thoracic and Mediastinal Disorders | bronchospasm; increased oral, pharyngeal and bronchial secretions; respiratory arrest; respiratory depression
Skin and Sub-cutaneous Tissue Disorders | rash, urticaria
Gastrointestinal Disorders | bowel cramps, diarrhea, flatulence, increased peristalsis
Renal and Urinary Disorders | urinary frequency
Musculoskeletal and Connective Tissue Disorders | arthralgia, muscle cramps, spasms, weakness
Miscellaneous | diaphoresis, flushing

Glycopyrrolate

The following adverse events have been identified during post-approval use of glycopyrrolate. Because these reactions are reported voluntarily from a population of uncertain size, it is not always possible to reliably estimate their frequency or establish a causal relationship to drug exposure:

System Organ Class | Adverse Reaction
Cardiovascular Disorders | cardiac arrhythmias (including bradycardia, ventricular tachycardia, ventricular fibrillation), cardiac arrest, hypertension, hypotension, heart block and QTc interval prolongation
Respiratory, Thoracic and Mediastinal Disorders | respiratory arrest
Injection site reactions | pruritus, edema, erythema, and pain at injection site
Miscellaneous | malignant hyperthermia

Glycopyrrolate is chemically a quaternary ammonium compound; hence, its passage across lipid membranes, such as the blood-brain barrier is limited. For this reason, the occurrence of CNS-related side effects is lower, in comparison to their incidence following administration of anticholinergics which are chemically tertiary amines that can cross this barrier readily.

7 DRUG INTERACTIONS

Neostigmine Methylsulfate
The pharmacokinetic interaction between neostigmine methylsulfate and other drugs has not been studied. Neostigmine methylsulfate is metabolized by microsomal enzymes in the liver. Use with caution when using neostigmine methylsulfate with other drugs which may alter the activity of metabolizing enzymes or transporters.
Glycopyrrolate
The concurrent use of glycopyrrolate with other anticholinergics or medications with anticholinergic activity, such as phenothiazines, antiparkinson drugs, or tricyclic antidepressants, may intensify the antimuscarinic effects and may result in an increase in anticholinergic side effects.

8 USE IN SPECIFIC POPULATIONS

8.1 Pregnancy

Risk Summary
Neostigmine Methylsulfate
There are no adequate or well-controlled studies of neostigmine in pregnant women. It is not known whether neostigmine can cause fetal harm when administered to a pregnant woman or can affect reproductive capacity. The incidence of malformations in human pregnancies has not been established for neostigmine as the data are limited. All pregnancies, regardless of drug exposure, have a background risk of 2 to 4% for major birth defects, and 15 to 20% for pregnancy loss.
No adverse effects were noted in rats or rabbits treated with human equivalent doses of neostigmine methylsulfate doses up to 8.1 and 13 mcg/kg/day, respectively, during organogenesis (0.1 to 0.2-times the maximum recommended human dose of 5 mg/60 kg person/day based on body surface area comparisons).
Anticholinesterase drugs, including neostigmine may cause uterine irritability and induce premature labor when administered to pregnant women near term.
Glycopyrrolate
Limited data available with glycopyrrolate use during pregnancy have not identified a drug-associated risk of birth defects and miscarriage, however, most of the reported exposures occurred after the first trimester. Most of the available data are based on studies with exposures that occurred at the time of Cesarean-section delivery, and these studies have not identified an adverse effect on maternal outcomes or infant Apgar scores (see Data).
In animal reproduction studies in pregnant rats and rabbits administered glycopyrrolate orally (rats) and intramuscularly (rabbits) during the period of organogenesis, no teratogenic effects were seen at 640-times and 10-times the maximum recommended human dose (MRHD) of 1 mg (on a mg/m^2 basis), respectively (see Data).
The estimated background risk for major birth defects and miscarriage for the indicated population is unknown. All pregnancies have a background risk of birth defect, loss, or other adverse outcomes. In the U.S. general population, the estimated background risk of major birth defects and miscarriage in the clinically recognized pregnancies is 2-4% and 15-20%, respectively. PREVDUO@ should be only given to a pregnant woman if the benefit outweighs the risk.

Data
Human Data
Neostigmine Methylsulfate:
There are no adequate or well-controlled studies of neostigmine methylsulfate in pregnant women.
Glycopyrrolate:
Published, randomized, controlled trials over several decades, which compared the use of glycopyrrolate to another antimuscarinic agent in pregnant women during Cesarean section, have not identified adverse maternal or infant outcomes. In normal doses (0.004 mg/kg), glycopyrrolate does not appear to affect fetal heart rate or fetal heart rate variability to a significant degree. Concentrations of glycopyrrolate in umbilical venous and arterial blood and in the amniotic fluid are low after intramuscular administration to parturients. Therefore, glycopyrrolate does not appear to penetrate through the placental barrier in significant amounts.
There are no studies on the safety of glycopyrrolate exposure during the period of organogenesis, and therefore, it is not possible to draw any conclusions on the risk of birth defects following exposure to glycopyrrolate during pregnancy. In addition, there are no data on the risk of miscarriage following fetal exposure to glycopyrrolate.
Animal Data
Neostigmine Methylsulfate:
In embryofetal development studies, rats and rabbits were administered neostigmine methylsulfate at human equivalent doses (HED, on a mg/m^2 basis) of 1.6, 4 and 8.1 mcg/kg/day 3.2, 8.1, and 13 mcg/kg/day, respectively, during the period of organogenesis (Gestation Days 6 through 17 for rats and Gestation Days 6 through 18 for rabbits). There was no evidence for a teratogenic effect in rats and rabbits up to HED 8.1 and 13 mcg/kg/day, which are approximately 0.097-times and 0.16-times the MRHD of 5 mg/60 kg, respectively in the presence of minimal maternal toxicity (tremors, ataxia, and prostration). The studies resulted in exposures in the animals well below predicted exposures in humans.
In a pre- and postnatal development study in rats, neostigmine methylsulfate was administered to pregnant female rats at HED of 1.6, 4 and 8.1 mcg/kg/day from Day 6 of gestation through Day 20 of lactation, with weaning on Day 21. There were no adverse effects on physical development, behavior, learning ability, or fertility in the offspring occurred at HED doses up 8.1 mcg/kg/day which is 0.097-times the maximum recommended daily human dose (MRHD) of 5 mL/60 kg on a mg/m^2 basis in the presence of minimal maternal toxicity (tremors, ataxia, and prostration). The studies resulted in exposures in the animals well below predicted exposures in humans.
Glycopyrrolate:
Reproduction studies with glycopyrrolate were performed in rats at a dietary dose of approximately 65 mg/kg/day (exposure was approximately 640 times the MRHD of 1 mg on a mg/m^2 basis) and rabbits at intramuscular doses of up to 0.5 mg/kg/day (exposure was approximately 10 times the maximum recommended daily human dose on a mg/m^2 basis). These studies produced no teratogenic effects to the fetus.
A preclinical study on reproductive performance of rats given glycopyrrolate resulted in a decreased rate of conception and survival at weaning.

8.2 Lactation

Risk Summary
It is not known whether neostigmine methylsulfate and glycopyrrolate are excreted in human milk. As with other anticholinergics, glycopyrrolate may cause suppression of lactation. The developmental and health benefits of breast feeding should be considered along with the mother’s clinical need for PREVDUO@ and any potential adverse effects on the breastfed child from PREVDUO@ Injection or from the underlying maternal condition.

8.4 Pediatric Use

PREVDUO@ is not recommended to be used in pediatric patients less than 2 years of age, as the blood pressure in pediatric patients, particularly infants and neonates, is sensitive to changes in heart rate. In these patients, a formulation that allows for glycopyrrolate to be administered prior to neostigmine to lessen the probability of bradycardia and hypotension is recommended.
Neostigmine Methylsulfate
Recovery of neuromuscular activity occurs more rapidly with smaller doses of cholinesterase inhibitors in infants and children than in adults. However, infants and small children may be at greater risk of complications from incomplete reversal of neuromuscular blockade due to decreased respiratory reserve. The risks associated with incomplete reversal outweigh any risk from giving higher doses of neostigmine (up to 0.07 mg/kg or up to a total of 5 mg, whichever is less).
The dose of neostigmine required to reverse neuromuscular blockade in children varies between 0.03 mg - 0.07 mg/kg, the same dose range shown to be effective in adults, and should be selected using the same criteria as used for adult patients [see Clinical Pharmacology (12.3)].
Glycopyrrolate
Infants, patients with Down’s syndrome, and pediatric patients with spastic paralysis or brain damage may experience an increased response to anticholinergics, thus increasing the potential for side effects.
A paradoxical reaction characterized by hyperexcitability may occur in pediatric patients taking large doses of anticholinergics including glycopyrrolate. Infants and young children are especially susceptible to the toxic effects of anticholinergics.

8.5 Geriatric Use

Because elderly patients are more likely to have decreased renal function, PREVDUO@ should be used with caution and monitored for a longer period in elderly patients. The duration of action of PREVDUO@ is prolonged in the elderly; however, elderly patients also experience slower spontaneous recovery from neuromuscular blocking agents. Therefore, dosage adjustments are not generally needed in geriatric patients; however, they should be monitored for longer periods than younger adults to assure additional doses of PREVDUO@ are not required. The duration of monitoring should be predicated on the anticipated duration of action for the NMBA used on the patient.

8.6 Renal Impairment

Elimination half-life of neostigmine methylsulfate was prolonged in anephric patients compared to normal subjects. In one study glycopyrrolate was administered IV in uremic patients undergoing renal transplantation. The mean elimination half-life was significantly longer (46.8 minutes) than in healthy patients (18.6 minutes). The mean area-under-the-concentration-time curve (10.6 hr-μg/L), mean plasma clearance (0.43 L/hr/kg), and mean 3-hour urine excretion (0.7%) for glycopyrrolate were also significantly different than those of controls (3.73 hr-μg/L, 1.14 L/hr/kg, and 50%, respectively). These results suggests that, the renal elimination of glycopyrrolate may be severely impaired in patients with renal failure.
Although no adjustments to PREVDUO@ dosing appear to be warranted in patients with impaired renal function, they should be closely monitored to assure the effects of the neuromuscular blocking agent, particularly one cleared by the kidneys, do not persist beyond those of Neostigmine Methylsulfate and Glycopyrrolate. In this regard, the interval for re-dosing the neuromuscular blocking agent during the surgical procedure may be useful in determining whether, and to what extent, post-operative monitoring needs to be extended.

8.7 Hepatic Impairment

The pharmacokinetics of neostigmine methylsulfate in patients with hepatic impairment have not been studied. Neostigmine methylsulfate is metabolized by microsomal enzymes in the liver, while glycopyrrolate is mostly eliminated unchanged by the kidney. No adjustments to the dosing of PREVDUO@ appear to be warranted in patients with hepatic insufficiency. However, patients should be carefully monitored if hepatically cleared neuromuscular blocking agents were used during their surgical procedure as their duration of action may be prolonged by hepatic insufficiency. This could result in the effects of the neuromuscular blocking agent outlasting those of neostigmine methylsulfate. This same situation may arise if the neuromuscular blocking agent has active metabolites. In this regard, the interval for re-dosing the neuromuscular blocking agent during the surgical procedure may be useful in determining whether, and to what extent, post-operative monitoring needs to be extended.

10 OVERDOSAGE

Neostigmine Methylsulfate
Muscarinic symptoms (nausea, vomiting, diarrhea, sweating, increased bronchial and salivary secretions, and bradycardia) may appear with overdosage of neostigmine methylsulfate (cholinergic crisis), but are minimized by the presence of glycopyrrolate in the prefilled syringe. The possibility of iatrogenic overdose can be lessened by carefully monitoring the muscle twitch response to peripheral nerve stimulation. Should overdosage occur, ventilation should be supported by artificial means until the adequacy of spontaneous respiration is assured, and cardiac function should be monitored.
Overdosage of neostigmine methylsulfate can cause cholinergic crisis, which is characterized by increasing muscle weakness, and through involvement of the muscles of respiration, may result in death. Myasthenic crisis, due to an increase in the severity of the disease, is also accompanied by extreme muscle weakness and may be difficult to distinguish from cholinergic crisis on a symptomatic basis. However, such differentiation is extremely important because increases in the dose of neostigmine methylsulfate or other drugs in this class, in the presence of cholinergic crisis or of a refractory or “insensitive” state, could have grave consequences. The two types of crises may be differentiated by the use of edrophonium chloride as well as by clinical judgment.
Treatment of the two conditions differs radically. Whereas the presence of myasthenic crisis requires more intensive anticholinesterase therapy, cholinergic crisis calls for the prompt withdrawal of all drugs of this type.
Glycopyrrolate
If CNS symptoms (e.g., excitement, restlessness, convulsions, psychotic behavior) occur, physostigmine (which does cross the blood–brain barrier) may be used. Physostigmine 0.5 to 2 mg should be slowly administered intravenously and repeated as necessary up to a total of 5 mg in adults. Proportionately smaller doses should be used in pediatric patients.
To combat hypotension, administer IV fluids and/or pressor agents along with supportive care.
Fever should be treated symptomatically.
Following overdosage, a curare-like action may occur, i.e., neuromuscular blockade leading to muscular weakness and possible paralysis. In the event of a curare-like effect on respiratory muscles, artificial respiration should be instituted and maintained until effective respiratory action returns.

11 DESCRIPTION

PREVDUO@ (neostigmine methylsulfate and glycopyrrolate) injection is a clear colorless solution available as a prefilled syringe that contains a fixed dose combination of neostigmine methylsulfate, a cholinesterase inhibitor and glycopyrrolate, an anticholinergic agent, for intravenous administration.
PREVDUO@ is available as a sterile solution in 3 mL Prefilled Syringe. Each mL contains Neostigmine Methylsulfate USP (1 mg), Glycopyrrolate USP (0.2 mg), edetate disodium dihydrate USP (0.5 mg), sodium chloride USP (8 mg) in water for injection. The pH is adjusted, when necessary, with Hydrochloric acid/sodium hydroxide to achieve a value of 3.6.
Neostigmine Methylsulfate USP
Neostigmine methylsulfate, a cholinesterase inhibitor, is (m-hydroxyphenyl) trimethylammonium methylsulfate dimethylcarbamate. The molecular formula is C13H22N2O6S, a molecular weight is 334.39 g/mol and the following structural formula is:

Glycopyrrolate USP
Glycopyrrolate is a quaternary ammonium salt (anticholinergic agent) with a chemical name of 3[(cyclopentylhydroxyphenylacetyl)oxy]-1,1-dimethyl pyrrolidinium bromide. The molecular formula is C19H28BrNO3 and the molecular weight is 398.33 and the structural formula is:

12 CLINICAL PHARMACOLOGY

12.1 Mechanism of Action

Neostigmine methylsulfate, a component of PREVDUO@, is a competitive cholinesterase inhibitor. By reducing the breakdown of acetylcholine, neostigmine methylsulfate induces an increase in acetylcholine in the synaptic cleft which competes for the same binding site as nondepolarizing neuromuscular blocking agents and reverses the neuromuscular blockade.
Glycopyrrolate, like other anticholinergic (antimuscarinic) agents, inhibits the action of acetylcholine on structures innervated by postganglionic cholinergic nerves and on smooth muscles that respond to acetylcholine but lack cholinergic innervation. These peripheral cholinergic receptors are present in the autonomic effector cells of smooth muscle, cardiac muscle, the sinoatrial node, the atrioventricular node, exocrine glands and, to a limited degree, in the autonomic ganglia. Thus, it diminishes the volume and free acidity of gastric secretions and controls excessive pharyngeal, tracheal, and bronchial secretions.
Glycopyrrolate antagonizes muscarinic symptoms (e.g., bronchorrhea, bronchospasm, bradycardia, and intestinal hypermotility) induced by cholinergic drugs such as the anticholinesterases.

12.2 Pharmacodynamics

The addition of glycopyrrolate to neostigmine (in the PREVDUO@ prefilled syringe) mitigates neostigmine-induced bradycardia.
Neostigmine Methylsulfate
Neostigmine methylsulfate-induced increases in acetylcholine levels results in the potentiation of both muscarinic and nicotinic cholinergic activity. The resulting elevation of acetylcholine competes with nondepolarizing neuromuscular blocking agents to reverse neuromuscular blockade. Neostigmine methylsulfate does not readily cross the blood-brain barrier and, therefore, does not significantly affect cholinergic function in the central nervous system.
Glycopyrrolate
The highly polar quaternary ammonium group of glycopyrrolate limits its passage across lipid membranes, such as the blood-brain barrier, in contrast to highly non-polar tertiary amines which penetrate lipid barriers easily.
With intravenous injection, the onset of action is generally evident within one minute. The vagal blocking effects persist for 2 to 3 hours and the antisialagogue effects persist up to 7 hours, periods longer than for atropine.

12.3 Pharmacokinetics

Distribution
Neostigmine Methylsulfate
Following intravenous injection, the observed neostigmine methylsulfate volume of distribution is reported between 0.12 and 1.4 L/kg. Protein binding of neostigmine methylsulfate to human serum albumin ranges from 15 to 25%.
Glycopyrrolate
The mean volume of distribution of glycopyrrolate was estimated to be 0.42±0.22 L/kg.
Metabolism
Neostigmine Methylsulfate
Neostigmine methylsulfate is metabolized by microsomal enzymes in the liver.
Glycopyrrolate
While over 80% of glycopyrrolate is eliminated unchanged in urine and bile the in vivo metabolism of glycopyrrolate in humans has not been studied.
Elimination
Neostigmine Methylsulfate
Following intravenous injection, the reported elimination half-life of neostigmine methylsulfate is between 24 and 113 minutes. Total body clearance of neostigmine methylsulfate is reported between 1.14 and 16.7 mL/min/kg.
Glycopyrrolate
The mean clearance and mean half-life values were reported to be 0.54±0.14 L/kg/hr and 0.83±0.13 hr, respectively post IV administration. After IV administration of a 0.2 mg radiolabeled glycopyrrolate, 85% of dose recovered was recovered in urine 48 hours postdose and some of the radioactivity was also recovered in bile. After IM administration of glycopyrrolate to adults, the mean half-life value is reported to be between 0.55 to 1.25 hrs. The following table summarizes the mean and standard deviation of pharmacokinetic parameters from a study.

Group | t1/2 (hr) | Vss (L/kg) | CL (L/kg/hr) | Tmax (min) | Cmax (mcg/L) | AUC (mcg/L•hr)
(6 mcg/kg IV) | 0.83±0.27 | 0.42±0.22 | 0.54±0.14 | – | – | 8.64±1.49*
(8 mcg/kg IM) | – | – | – | 27.48±6.12 | 3.47±1.48 | 6.64±2.33*

*0-8 hr

Specific Populations

Renal Impairment

Neostigmine methylsulfate:

Elimination half-life of neostigmine methylsulfate was prolonged in anephric patients compared to normal subjects; the mean±SD elimination half-lives for normal, transplant and anephric patients were 79.8±48.6, 104.7±64 and 181±54 min, respectively.

Glycopyrrolate:
In one study glycopyrrolate was administered IV in uremic patients undergoing renal transplantation. The mean elimination half-life was significantly longer (46.8 minutes) than in healthy patients (18.6 minutes). The mean area-under-the-concentration-time curve (10.6 mcg*hr/L), mean plasma clearance (0.43 L/hr/kg), and mean 3-hour urine excretion (0.7%) for glycopyrrolate were also significantly different than those of controls (3.73 mcg*hr/L, 1.14 L/hr/kg, and 50%, respectively). These results suggest that the elimination of glycopyrrolate is severely impaired in patients with renal failure.
Hepatic Impairment
The pharmacokinetics of neither neostigmine methylsulfate nor glycopyrrolate have been studied in patients with hepatic impairment.
Pediatrics
Neostigmine Methylsulfate
The mean±SD elimination half-life of neostigmine methylsulfate in children (1-6 years) and adults (29-48 years) were 48±16 min and 67±8 min, respectively. The mean±SD observed neostigmine methylsulfate clearance for children and adults were 11±3 and 10±2 mL/min/kg (mean±SD), respectively.
Glycopyrrolate
Following IV administration (5 mcg/kg glycopyrrolate) to children, the mean half-life values were reported to be between 19.2 and 99.2 minutes.

13 NONCLINICAL TOXICOLOGY

13.1 Carcinogenesis, Mutagenesis, Impairment Of Fertility

Carcinogenesis
Neostigmine Methylsulfate
Long-term animal studies have not been performed to evaluate the carcinogenic potential of neostigmine.
Glycopyrrolate
Long-term studies in animals have not been performed to evaluate carcinogenic potential.
Genotoxicity
Neostigmine Methylsulfate
Neostigmine methylsulfate was not mutagenic or clastogenic when evaluated in an in vitro bacterial reverse mutation assay (Ames test), an in vitro Chinese hamster ovary cell chromosomal aberration assay, or an in vivo mouse bone marrow micronucleus assay.
Glycopyrrolate
Studies to evaluate the mutagenic potential of glycopyrrolate have not been conducted.
Impairment of Fertility
Neostigmine Methylsulfate
In a fertility and early embryonic development study in rats, male rats were treated for 28 days prior to mating and female rats were treated for 14 days prior to mating with intravenous neostigmine methylsulfate (human equivalent doses of 1.6, 4, and 8.1 mcg/kg/day, based on body surface area). No adverse effects were reported at any dose (up to 0.1-times the MRHD of 5 mg/60 kg person based on a body surface area comparison).
Glycopyrrolate
In reproduction studies in rats, dietary administration of glycopyrrolate resulted in diminished rates of conception in a dose-related manner. Other studies in dogs suggest that this may be due to diminished seminal secretion which is evident at high doses of glycopyrrolate.

14 CLINICAL STUDIES

The evidence for the efficacy of neostigmine methylsulfate for the reversal of the effects of nondepolarizing neuromuscular blocking agents after surgery is derived from the published literature. Randomized, spontaneous-recovery or placebo-controlled studies using similar efficacy endpoints evaluated a total of 404 adult and 80 pediatric patients undergoing various surgical procedures. Patients had reductions in their recovery time from neuromuscular blockade with neostigmine methylsulfate treatment compared to spontaneous recovery.

16 HOW SUPPLIED/STORAGE AND HANDLING

PREVDUO@ (neostigmine methylsulfate and glycopyrrolate) injection is a clear, colorless solution available in the following:

NDC No. | Strength | Pack Size
42023-269-05 | 1 mg of Neostigmine Methylsulfate USP and 0.2 mg of Glycopyrrolate USP per mL | 5 X 3 mL prefilled syringe in one carton
42023-269-01 | 1 mg of Neostigmine Methylsulfate USP and 0.2 mg of Glycopyrrolate USP per mL | 3 mL Single dose prefilled syringe

PREVDUO@ (neostigmine methylsulfate and glycopyrrolate) injection should be stored at 20°C to 25°C (68°F to 77°F); excursions permitted to 15°C to 30°C (59°F to 86°F) [see USP Controlled Room Temperature]. Protect from light. Store in carton until time of use.

17 PATIENT COUNSELING INFORMATION

Increased Intraocular Pressure: Glycopyrrolate in the PREVDUO@ may cause mydriasis and increase intraocular pressure in patients with glaucoma. Advise patients with glaucoma to promptly seek medical care in the event that they experience symptoms of acute angle closure glaucoma (pain and reddening of the eyes, accompanied by dilated pupils) [see Warnings and Precautions (5.6)].
Drowsiness and Blurred Vision: Inform patients that PREVDUO@ may cause drowsiness or blurred vision. Warn patients not to operate a motor vehicle or other machinery or perform hazardous work until these issues resolve. [see Warnings and Precautions (5.7)].
PREVDUO@ is a registered trademark of Slayback Pharma LLC.
Manufactured for:
Endo USA
Malvern, PA 19355

Revised: 04/2024

PACKAGE LABEL.PRINCIPAL DISPLAY PANEL

CONTAINER LABEL

PREVDUO@ (neostigmine methylsulfate and glycopyrrolate) Injection

1 mg/mL of Neostigmine Methylsulfate and 0.2 mg/mL of Glycopyrrolate in 3 mL Prefilled Syringe

NDC 42023-269-01

Rx Only